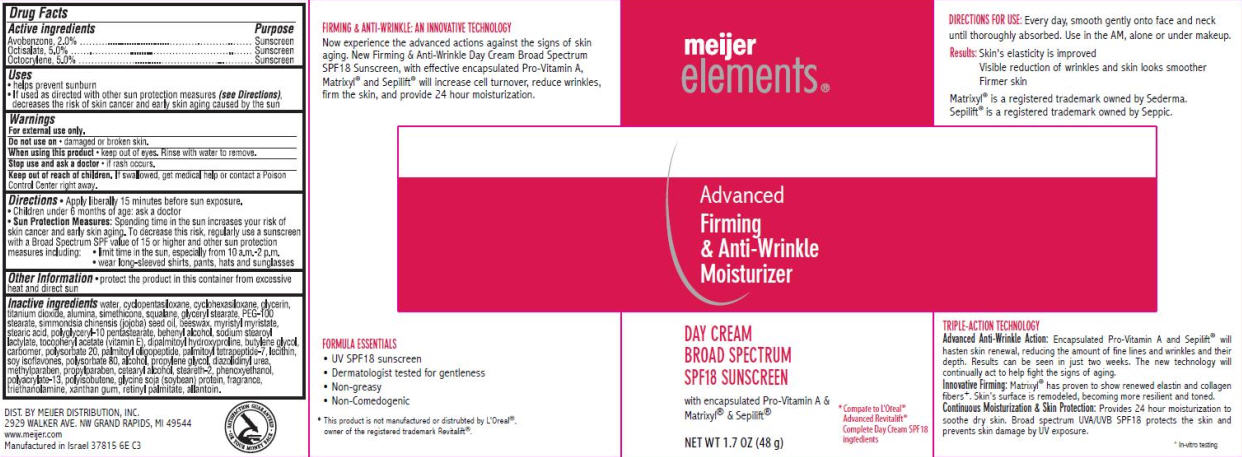 DRUG LABEL: Meijer Elements Advanced Firming and Anti-Wrinkle
NDC: 41250-263 | Form: CREAM
Manufacturer: Meijer Distribution Inc.
Category: otc | Type: HUMAN OTC DRUG LABEL
Date: 20120511

ACTIVE INGREDIENTS: AVOBENZONE 2 g/100 g; OCTISALATE 5 g/100 g; OCTOCRYLENE 5 g/100 g
INACTIVE INGREDIENTS: WATER; CYCLOMETHICONE 5; CYCLOMETHICONE 6; GLYCERIN; TITANIUM DIOXIDE; ALUMINUM OXIDE; DIMETHICONE; SQUALANE; GLYCERYL MONOSTEARATE; PEG-100 STEARATE; JOJOBA OIL; YELLOW WAX; MYRISTYL MYRISTATE; STEARIC ACID; DOCOSANOL; SODIUM STEAROYL LACTYLATE; .ALPHA.-TOCOPHEROL ACETATE; DIPALMITOYL HYDROXYPROLINE; BUTYLENE GLYCOL; CARBOMER 1342; POLYSORBATE 20; PALMITOYL OLIGOPEPTIDE; PALMITOYL TETRAPEPTIDE-7; LECITHIN, SOYBEAN; SOY ISOFLAVONES; POLYSORBATE 80; ALCOHOL; PROPYLENE GLYCOL; DIAZOLIDINYL UREA; METHYLPARABEN; PROPYLPARABEN; CETOSTEARYL ALCOHOL; STEARETH-2; PHENOXYETHANOL; POLYISOBUTYLENE (1000 MW); SOYBEAN; TROLAMINE; XANTHAN GUM; VITAMIN A PALMITATE; ALLANTOIN

meijer elelments® Advanced Firming and Anti-Wrinkle Moisturizer Day Cream Broad Spectrum SPF18 Sunscreen

Active ingredient

Avobenzone 2.0%

Octisalate 5.0%

Octocrylene 5.0%

Purpose

Sunscreen

Uses

- helps prevent sunburn
- If used as directed with other sun protection measures (see Directions), decreases the risk of skin cancer and early skin aging caused by the sun

Warnings

For external use only.

Do not use on

- damaged or broken skin.

When using this product

- keep out of eyes. Rinse with water to remove.

Stop use and ask a doctor

- if rash occurs.

Keep Out of Reach of Children.

If swallowed, get medical help or contact a Poison Control Center right away.

Directions

- Apply liberally 15 minutes before sun exposure.
- Children under 6 months of age: ask a doctor
- Sun Protection Measures: Spending time in the sun increases your risk of skin cancer and early skin aging. To decrease this risk, regularly use a sunscreen with a Broad Spectrum SPF value of 15 or higher and other sun protection measures including:
  - limit time in the sun, especially from 10 a.m. - 2 p.m.
  - wear long-sleeved shirts, pants, hats and sunglasses

Other Information

- protect the product in this container from excessive heat and direct sun

Inactive Ingredients

water, cyclopentasiloxane, cyclohexasiloxane, glycerin, titanium dioxide, alumina, simethicone, squalane, glyceryl stearate, PEG-100 stearate, simmondsia chinensis (jojoba) seed oil, beeswax, myristyl myristate, stearic acid, polyglyceryl-10 pentastearate, bhenyl alcohol, sodium steroyl lactylate, tocopheryl acetate (vitamin E), dipalmitoyl hydroxyproline, butylene glycol, carbomer, polysorbate 20, palmitoyl oiligopeptide, palmitoyl tetrapeptide-7, lecithin, soy isoflavones, polysorbate 80, alcohol, propylene glycol, diazolidinyl urea, methylparaben, propylparaben, cetearyl alcohol, steareth-2, phenoxyethanol, polyacrylate-13, polyisobutene, glycine soja (soybean) protein, fragrance, triethanolamine, xanthan gum, retinyl palmitate, allantoin.

Package/Label Principal Display Panel

meijer elements®
Advanced Firming & Anti-Wrinkle Moisturizer

Day Cream Broad Spectrum SPF18 Sunscreen

with encapsulated Pro-Vitamin A & Matrixyl® & Sepilift®

*Complare to L'Oreal® Advanced Revitalift® Complete Day Cream SPF18 ingredients

NET WT 1.7 OZ (48 g)

DIST. BY MEIJER
DISTRIBUTION, INC.
2929 WALKER AVE. NW
GRAND RAPIDS, MI 49544
www.meijer.com
Manufactured in Israel
2F692 6E C4

Carton Label